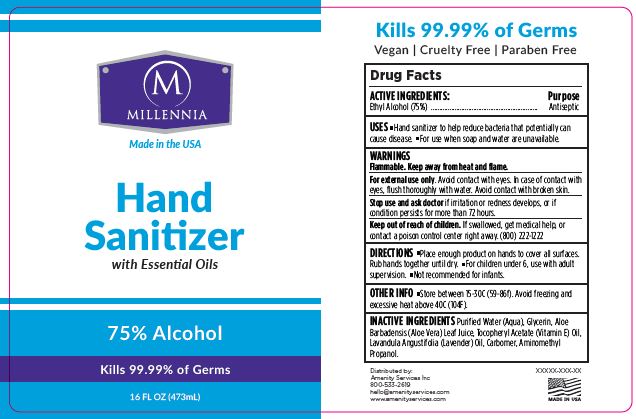 DRUG LABEL: Hand Sanitizer
NDC: 79185-101 | Form: GEL
Manufacturer: Amenity Services, Inc.
Category: otc | Type: HUMAN OTC DRUG LABEL
Date: 20200623

ACTIVE INGREDIENTS: ALCOHOL 75 mL/100 mL
INACTIVE INGREDIENTS: WATER; GLYCERIN; ALOE VERA LEAF; .ALPHA.-TOCOPHEROL ACETATE; LAVENDER OIL; CARBOMER HOMOPOLYMER, UNSPECIFIED TYPE; AMINOMETHYLPROPANOL

Millenia Hand Sanitizer - 75% Alcohol

ACTIVE INGREDIENT

Ethyl Alcohol (75%)

PURPOSE

ANTISEPTIC

USE

- Hand sanitizer to help reduce bacteria that potentially can cause disease.
- For use when soap and water are unavailable.

WARNINGS

Flammable. Keep away from heat and flame.

For external use only. Avoid contact with eyes. In case of contact with eyes, flush thoroughly with water. Avoid contact with broken skin.

Stop use and ask doctor if irritation or redness develops, or if condition persists for more than 72 hours.

Keep out of reach of children.

If swallowed, get medical help or contact a Poison Control Center right away.

DIRECTIONS

- Place enough product on hands to cover all surfaces. Rub hands together until dry.
- For children under 6, use with adult supervision.
- Not recommended for infants.

INACTIVE INGREDIENTS

Purified Water (Aqua), Glycerin, Aloe Barbadensis (Aloe Vera) Leaf Juice, Tocopheryl Acetate (Vitamin E) Oil, Lavandula Angustifolia (Lavender) Oil, Carbomer, Aminomethyl Propanol.

OTHER INFORMATION

- Store between 15-30C (59-86f). Avoid freezing and excessive heat above 40C (104F).